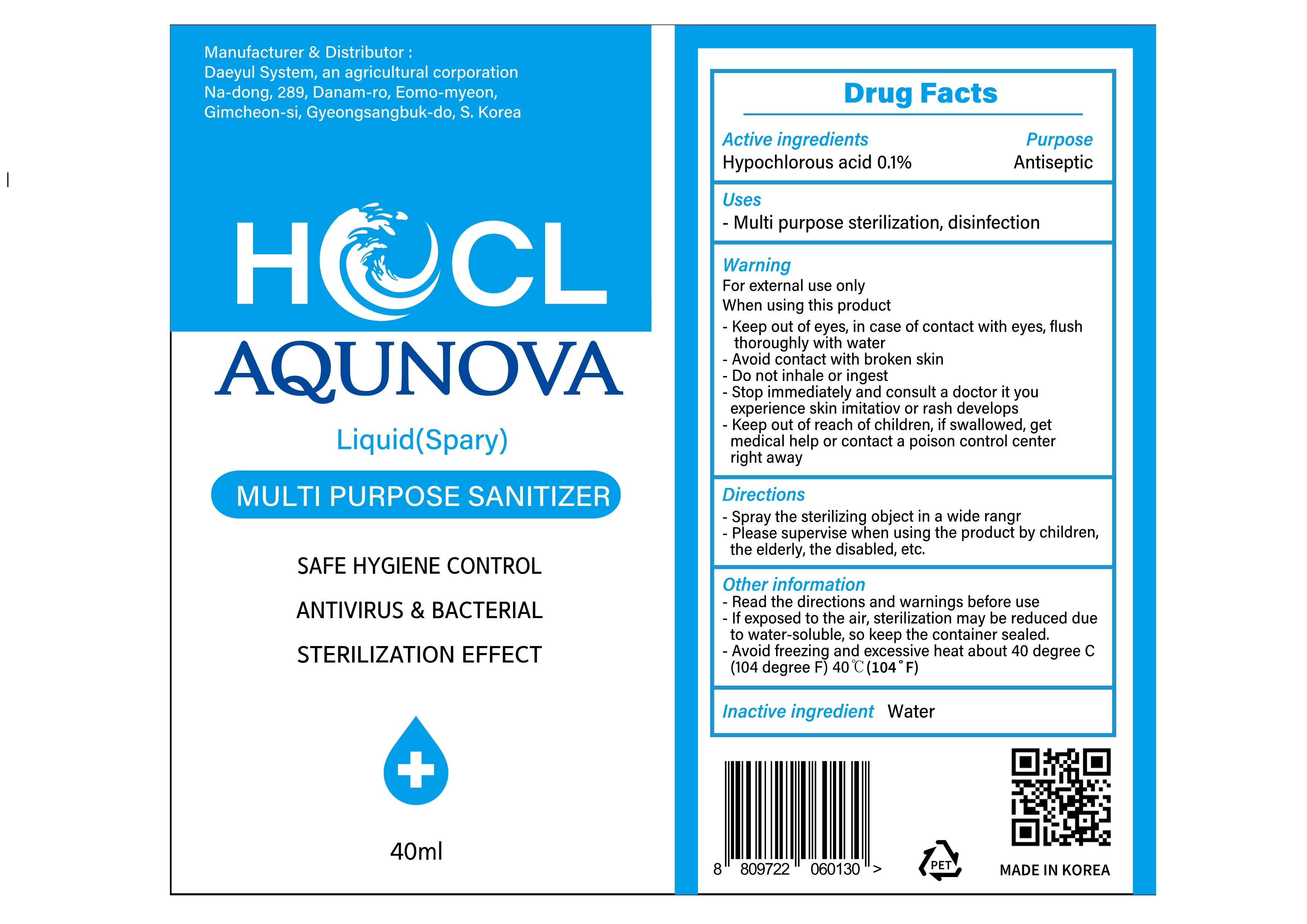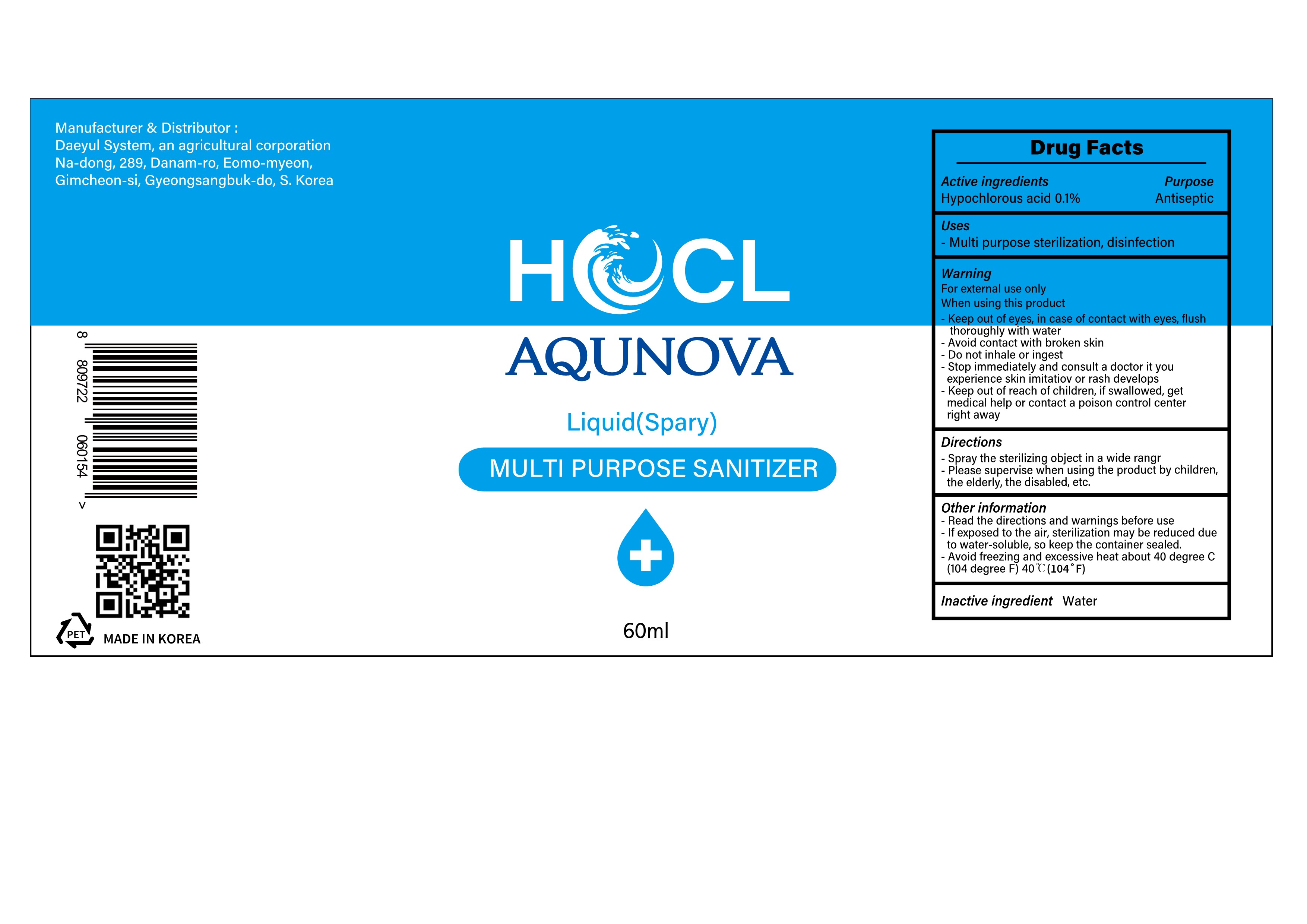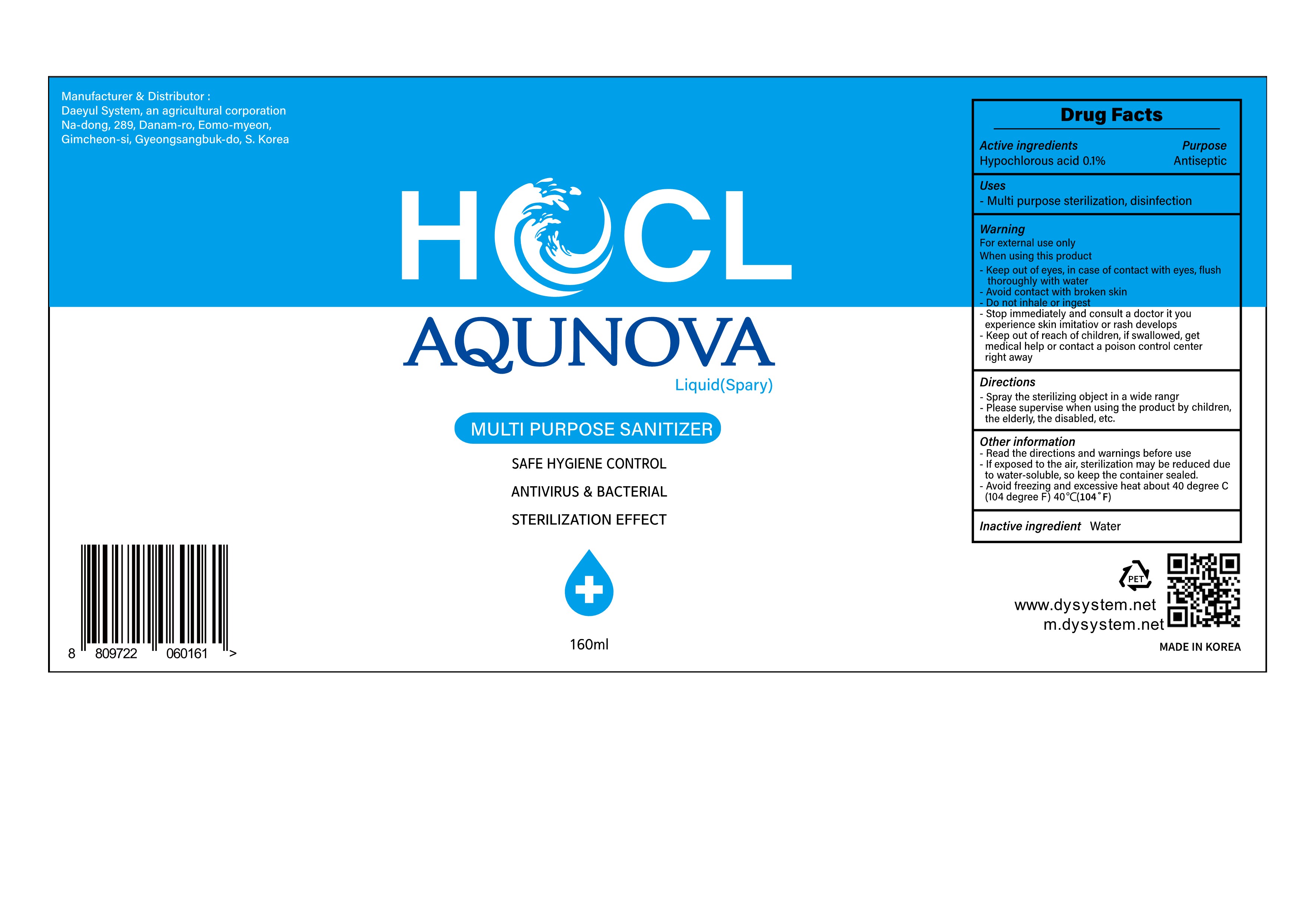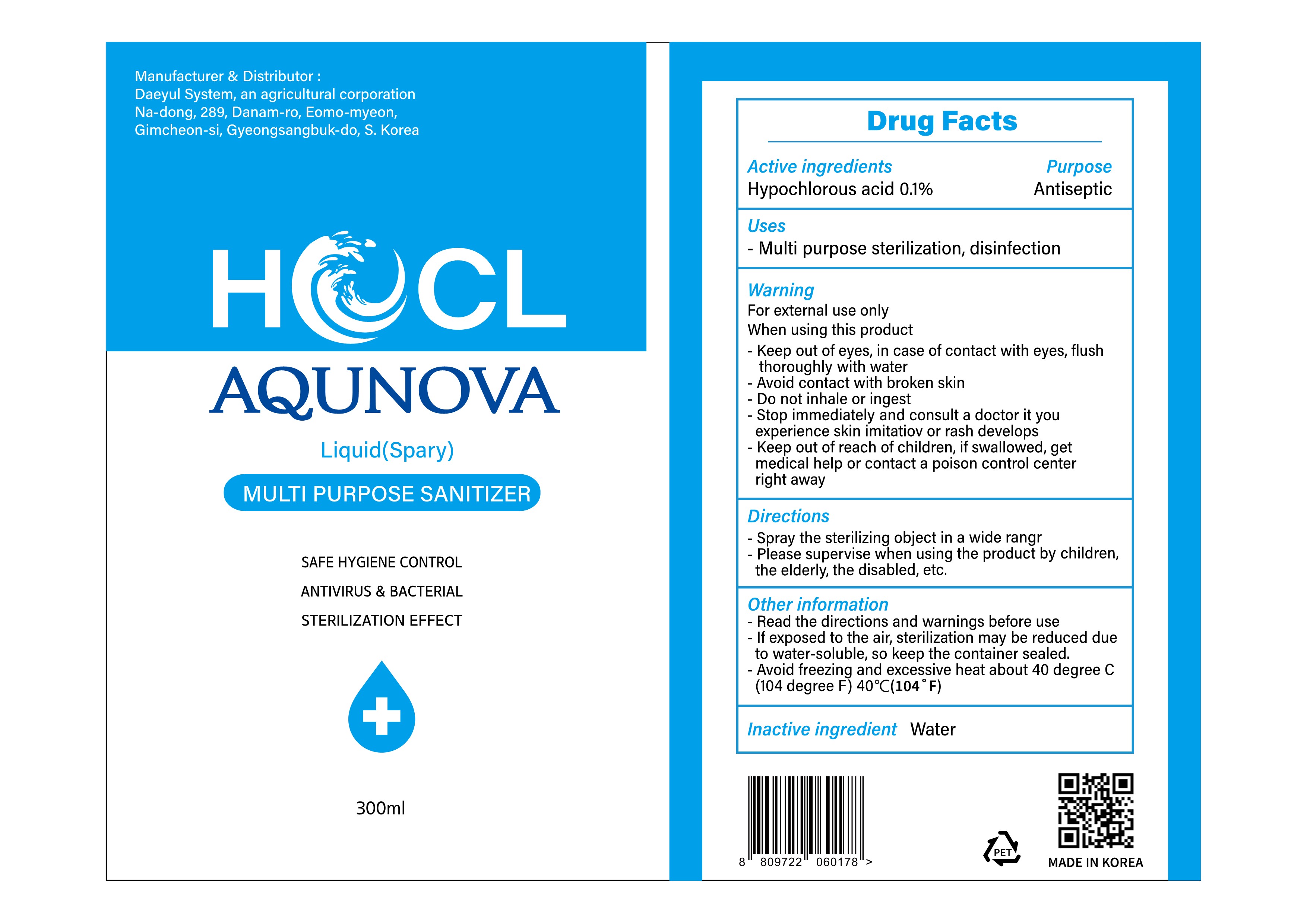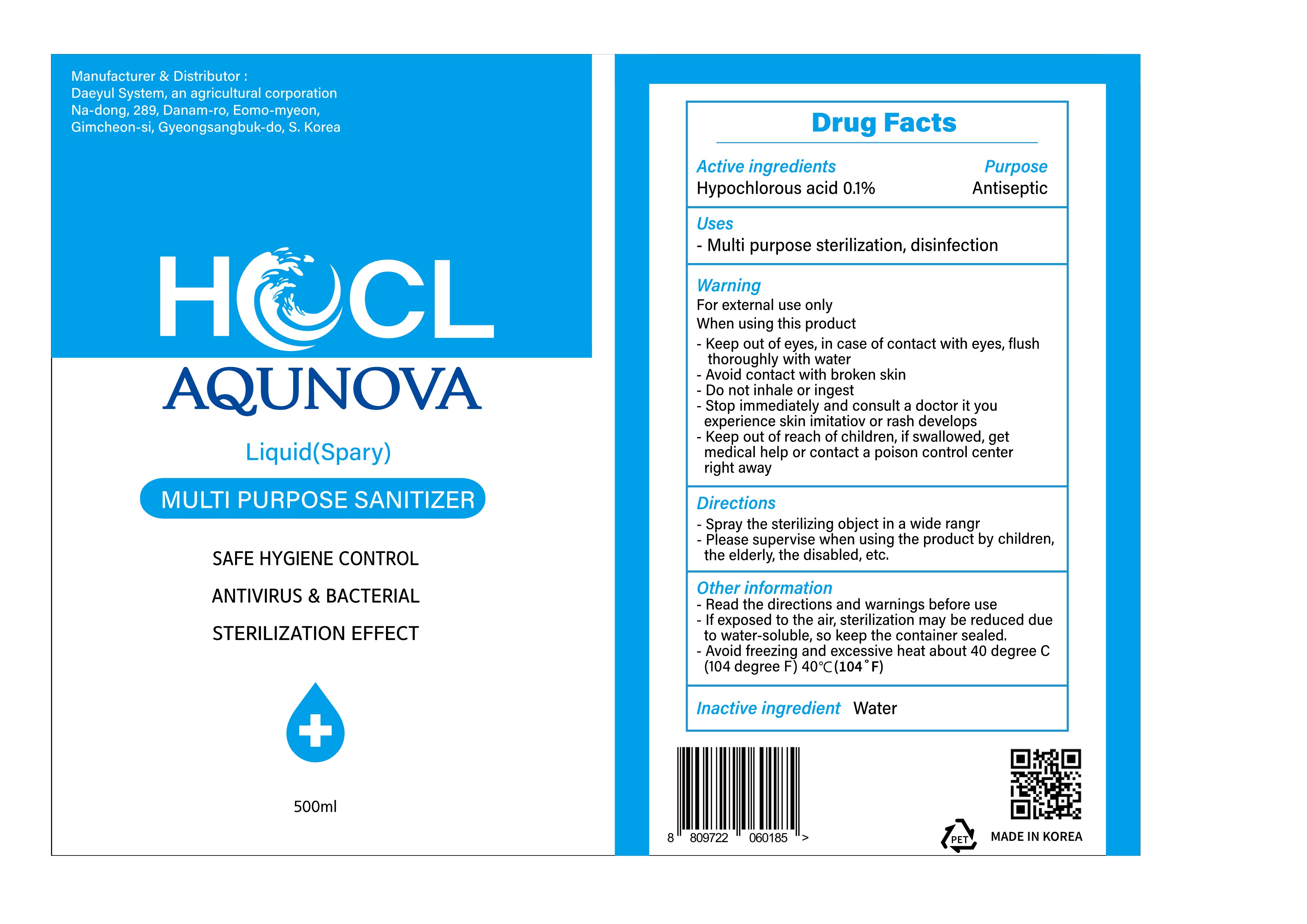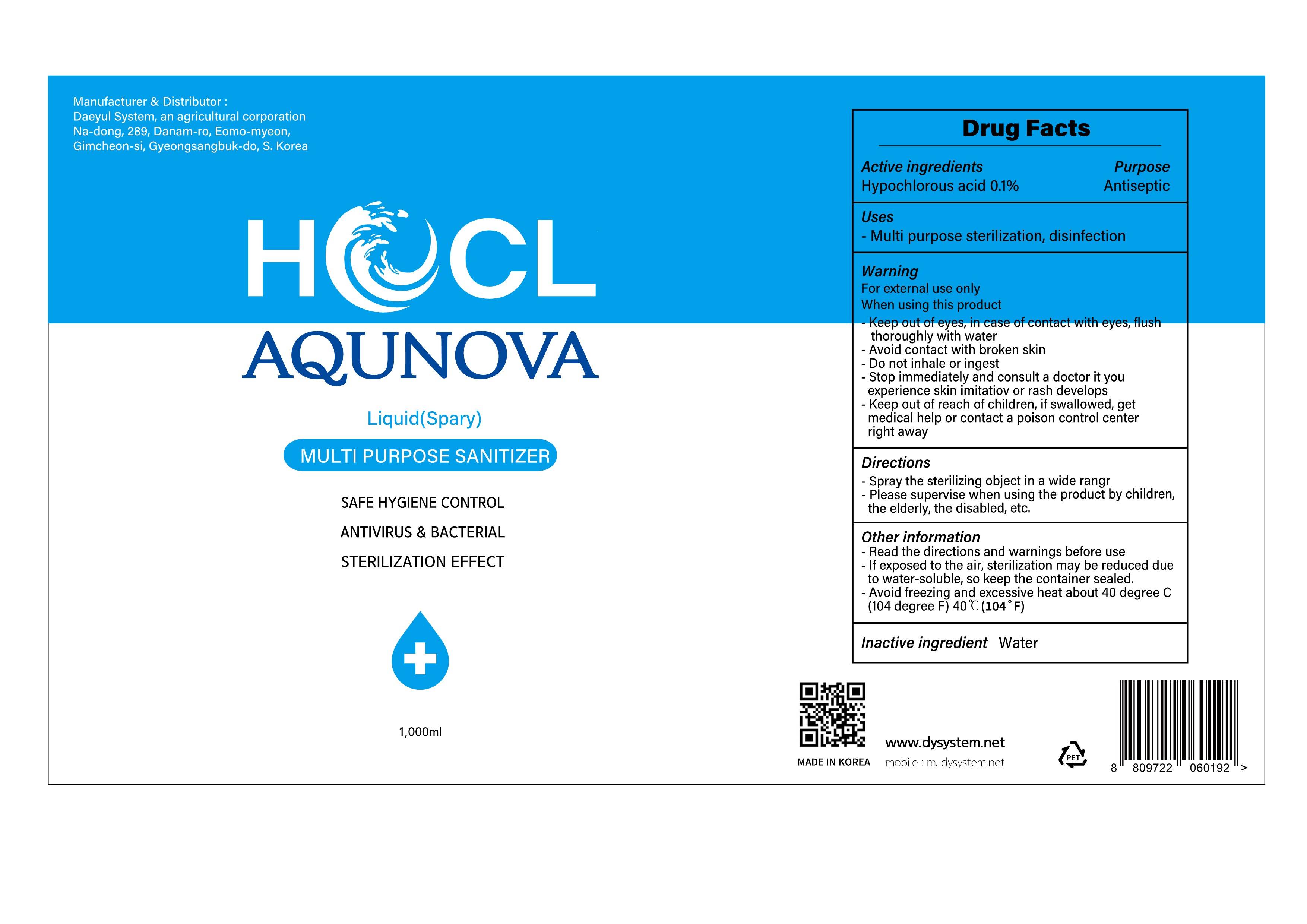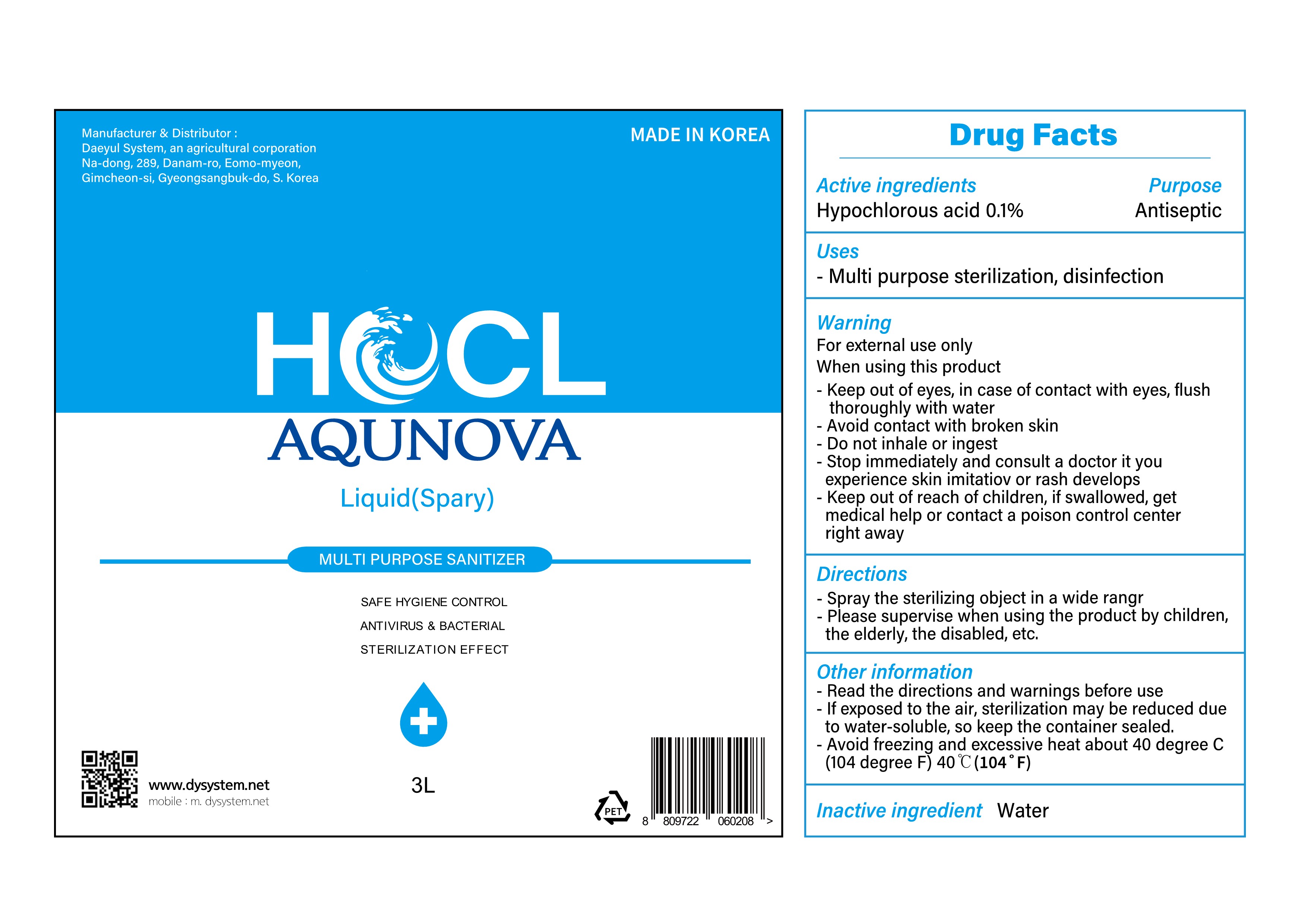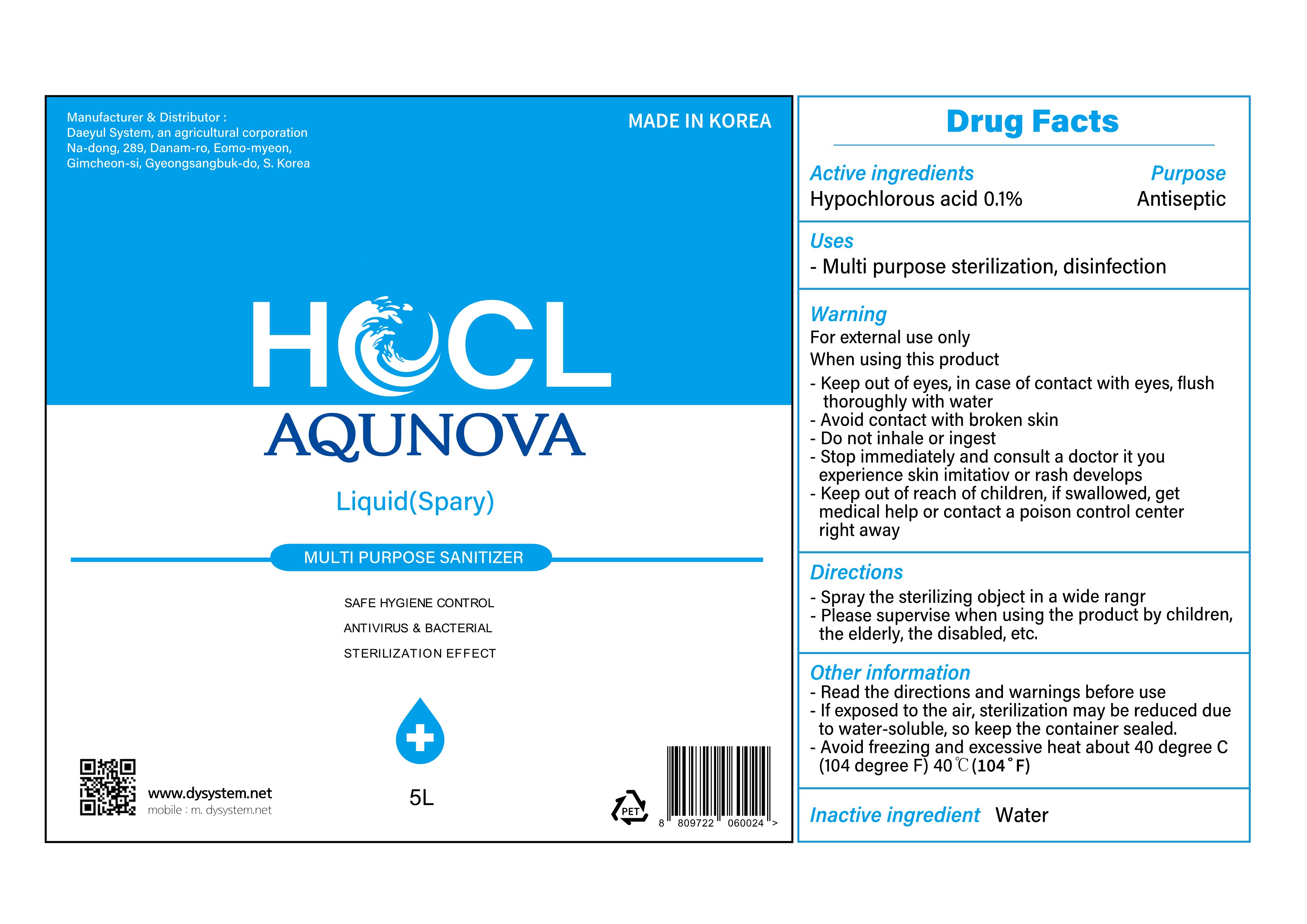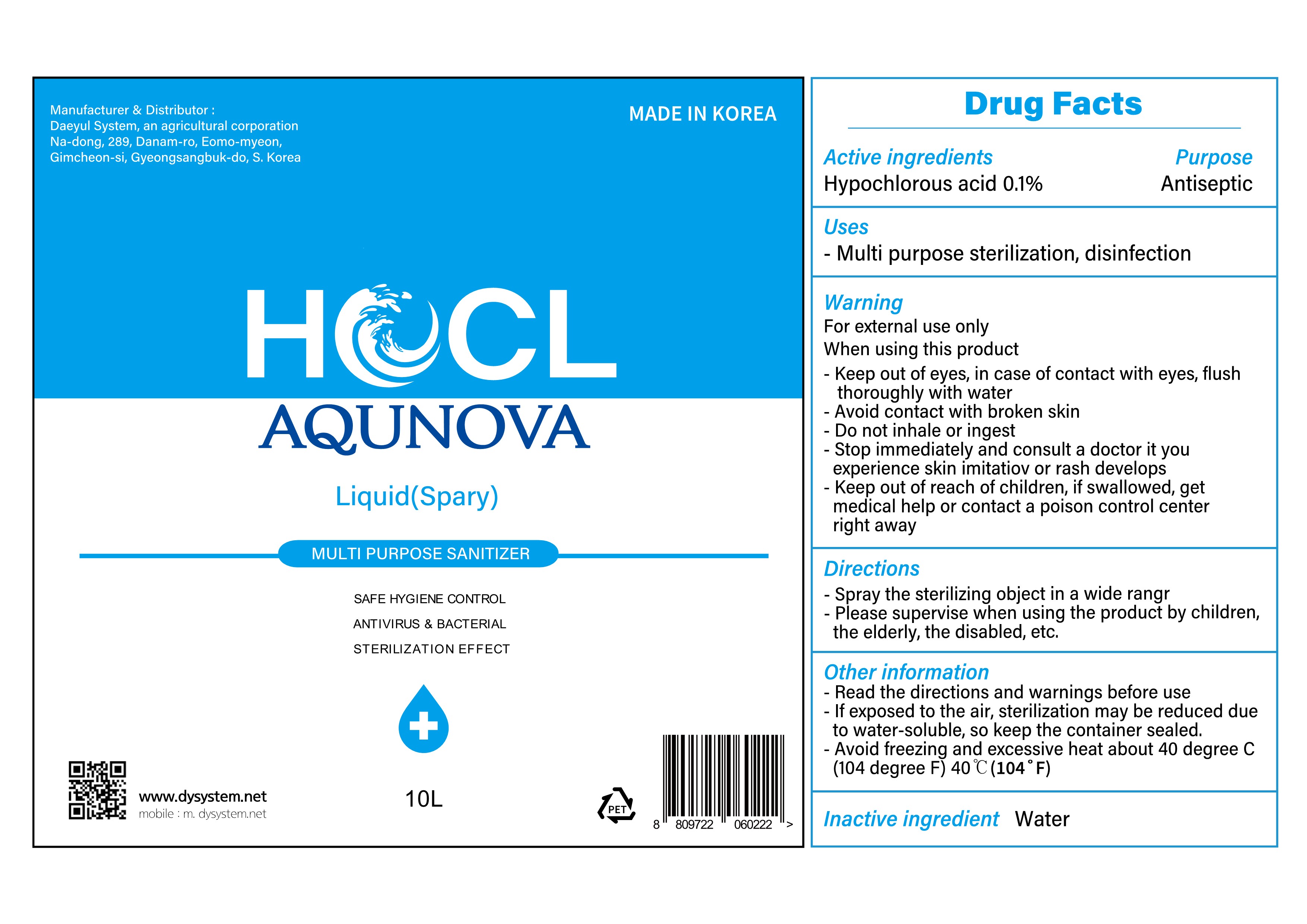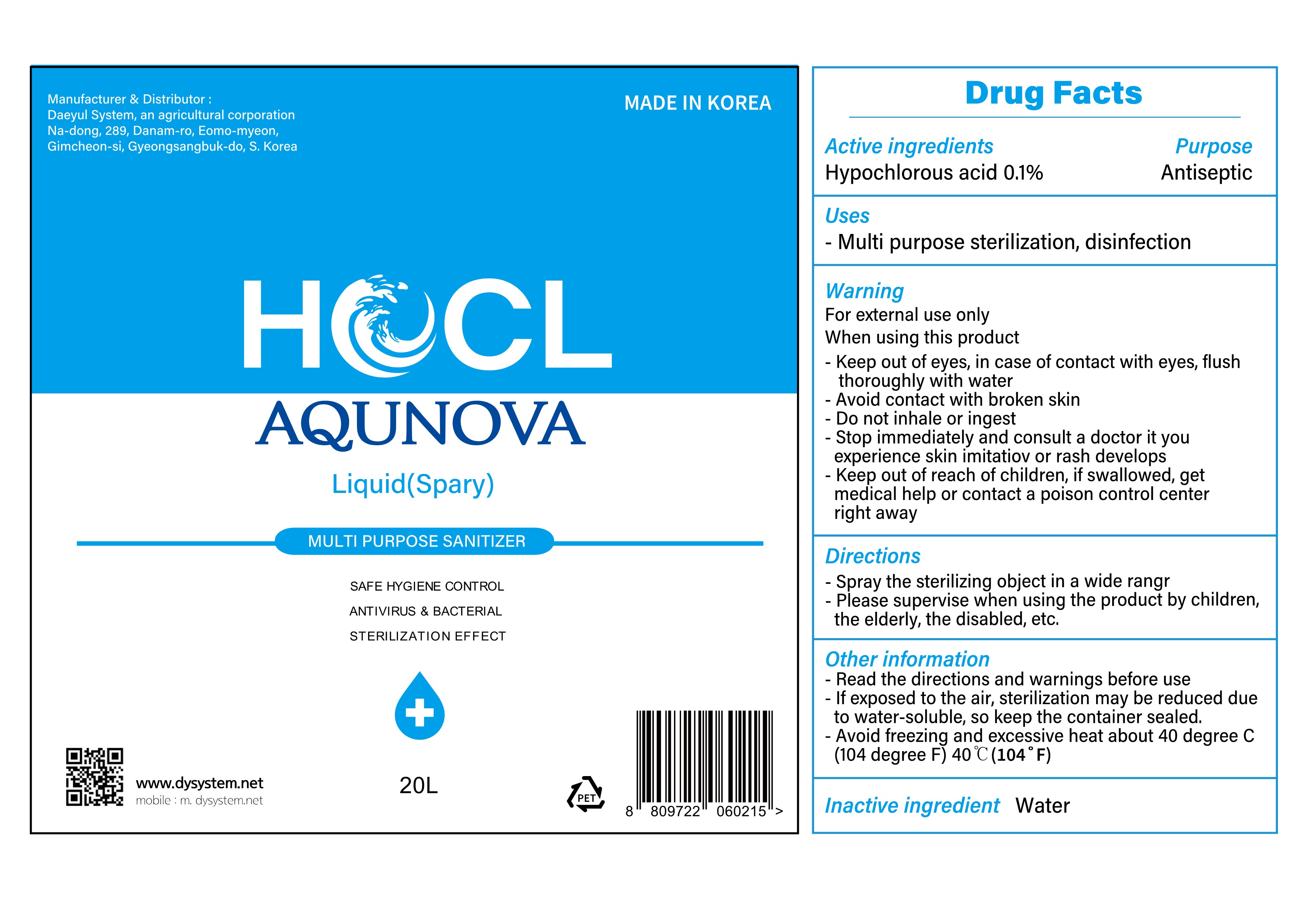 DRUG LABEL: AQUNOVA. WATER INNOVATION
NDC: 80542-201 | Form: LIQUID
Manufacturer: Agricultural Company Corporation, Inc
Category: otc | Type: HUMAN OTC DRUG LABEL
Date: 20200911

ACTIVE INGREDIENTS: HYPOCHLOROUS ACID 0.1 g/100 mL
INACTIVE INGREDIENTS: WATER

80542-201

ACTIVE INGREDIENTS

Hypochlorous Acid 0.1%

PURPOSE

Antiseptic

USES

Multi purpose sterilization, disinfection

WARNINGS

For external use only

When using this product

- Keep out of eyes. In case of contact with eyes, flush thoroughly with water.

- Avoid contact with broken skin.

- Do not inhale or ingest.

WARNINGS

- Stop immediately and consult a doctor it you experience skin imitation or rash develops.

WARNINGS

- Keep out of reach of children. If swallowed, get medical help or contact a Poison Control Center right away.

DIRECTIONS

- Spray the sterilizing object in a wide range

- Please supervise when using the product by children, the elderly, the disabled, etc.

OTHER INFORMATION

- Read the directions and warmings before use

- If exposed to the air, sterilization may be reduced due to water-soluble, so keep the container sealed.

- Avoid freezing and excessive heat above 40 degreee C (104 degree F) 40C(104F)

INACTIVE INGREDIENTS

Water